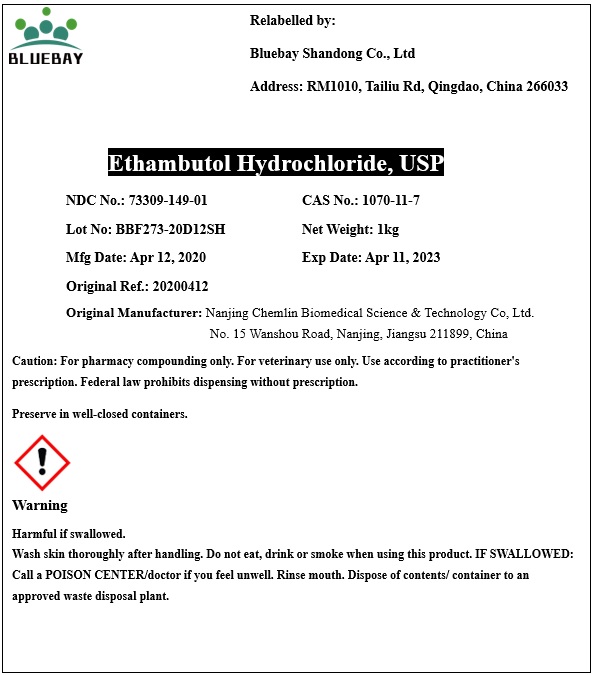 DRUG LABEL: Ethambutol Hydrochloride
NDC: 73309-149 | Form: POWDER
Manufacturer: BLUEBAY SHANDONG CO.,LTD
Category: other | Type: BULK INGREDIENT
Date: 20200623

ACTIVE INGREDIENTS: ETHAMBUTOL HYDROCHLORIDE 1 kg/1 kg

Ethambutol Hydrochloride